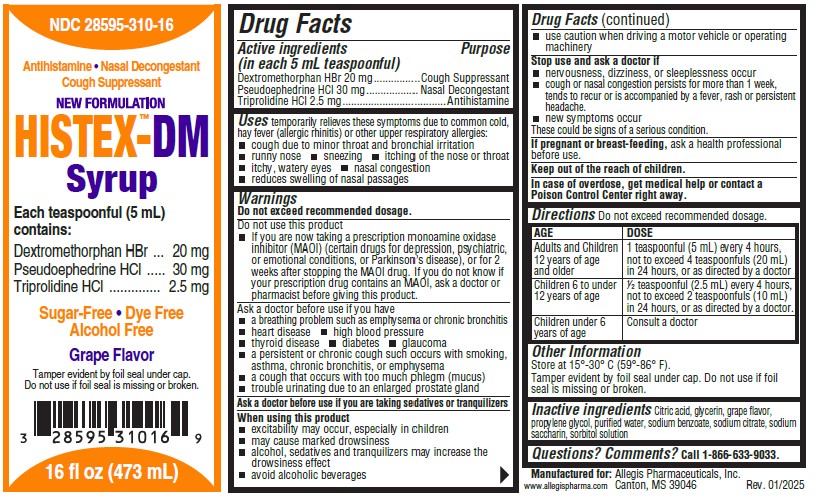 DRUG LABEL: HISTEX-DM New Formulation
NDC: 28595-310 | Form: SYRUP
Manufacturer: Allegis Pharmaceuticals, LLC
Category: otc | Type: HUMAN OTC DRUG LABEL
Date: 20250310

ACTIVE INGREDIENTS: DEXTROMETHORPHAN HYDROBROMIDE 20 mg/5 mL; PSEUDOEPHEDRINE HYDROCHLORIDE 30 mg/5 mL; TRIPROLIDINE HYDROCHLORIDE 2.5 mg/5 mL
INACTIVE INGREDIENTS: CITRIC ACID MONOHYDRATE; GLYCERIN; PROPYLENE GLYCOL; WATER; SODIUM CITRATE, UNSPECIFIED FORM; SACCHARIN SODIUM; SORBITOL; SODIUM BENZOATE; GRAPE

HISTEX™-DM Syrup New Formulation

Drug Facts

ACTIVE INGREDIENT

Active ingredients (in each 5 mL teaspoonful) | Purpose
Dextromethorphan HBr 20 mg | Cough Suppressant
Pseudoephedrine HCI 30 mg | Nasal Decongestant
Triprolidine HCl 2.5 mg | Antihistamine

Uses

temporarily relieves these symptoms due to common cold, hay fever (allergic rhinitis) or other upper respiratory allergies:

- cough due to minor throat or bronchial irritation
- runny nose
- sneezing
- itching of the nose or throat
- itchy, watery eyes
- nasal congestion
- reduces swelling of nasal passages

Warnings

Do not exceed recommended dosage.

Do not use this product

- If you are now taking a prescription monoamine oxidase inhibitor (MAOI) (certain drugs for depression, psychiatric, or emotional conditions, or Parkinson's disease), or for 2 weeks after stopping the MAOI drug. If you do not know if your prescription drug contains an MAOI, ask a doctor or pharmacist before giving this product.

Ask a doctor before use if you have

- a breathing problem such as emphysema or chronic bronchitis
- heart disease
- high blood pressure
- thyroid disease
- diabetes
- glaucoma
- a persistent or chronic cough such occurs with smoking, asthma, chronic bronchitits, or emphysema
- a cough that occurs with too much phlegm (mucus)
- trouble urinating due to an enlarged prostate gland

Ask a doctor before use if you are taking sedatives or tranquilizers

When using this product

- excitability may occur, especially in children
- may cause drowsiness
- alcohol, sedatives and tranquilizers may increase the drowsiness effect
- avoid alcoholic beverages
- use caution when driving a motor vehicle or operating machinery

Stop use and ask a doctor if

- nervousness, dizziness, or sleeplessness occur
- cough or nasal congestion persists for more than 1 week, tends to recur or is accompanied by a fever, rash or persistent headache.
- new symptoms occur

These could be signs of a serious condition.

PREGNANCY OR BREAST FEEDING

If pregnant or breast-feeding, ask a health professional before use.

Keep out of the reach of children.

In case of overdose, get medical help or contact a Poison Control Center right away.

Directions

Do not exceed recommended dosage.

AGE | DOSE
Adults and Children 12 years of age and older: | 1 teaspoonful (5 mL) every 4 hours, not to exceed 4 teaspoonfuls (20 mL) in 24 hours, or as directed by a doctor
Children 6 to under 12 years of age | ½ teaspoonful (2.5 mL) every 4 hours, not to exceed 2 teaspoonfuls (10 mL) in 24 hours, or as directed by a doctor.
Children under 6 years of age | Consult a doctor

Other Information

Store at 15°-30° C (59°-86° F).

Tamper evident by foil seal under cap. Do not use if foil seal is missing or broken.

Inactive ingredients

Citric Acid, Glycerin, Grape Flavor, Propylene Glycol, Purified Water, Sodium Bensoate, Soduim Citrate, Sodium Saccharin, Sorbitol Solution.

Questions? Comments?

Call 1-866-633-9033.

Manufactured for: Allegis Pharmaceuticals, Inc.

Canton MS 39046

www.allegispharma.com

Rev. 01/2025

PRINCIPAL DISPLAY PANEL - 473 mL Bottle Label

NDC 28595-310-16

Antihistamine - Nasal Decongestant - Cough Suppressant

HISTEX™-DM New Formulation
Syrup

Each teaspoonful (5 mL)
contains:
Dextromethorphan HBr 20 mg
Pseudoephedrine HCI 30mg
Triprolidine HCl 2.5 mg

Sugar-Free - Dye Free - Alcohol Free

Grape Flavor

16 fl oz (473 mL)